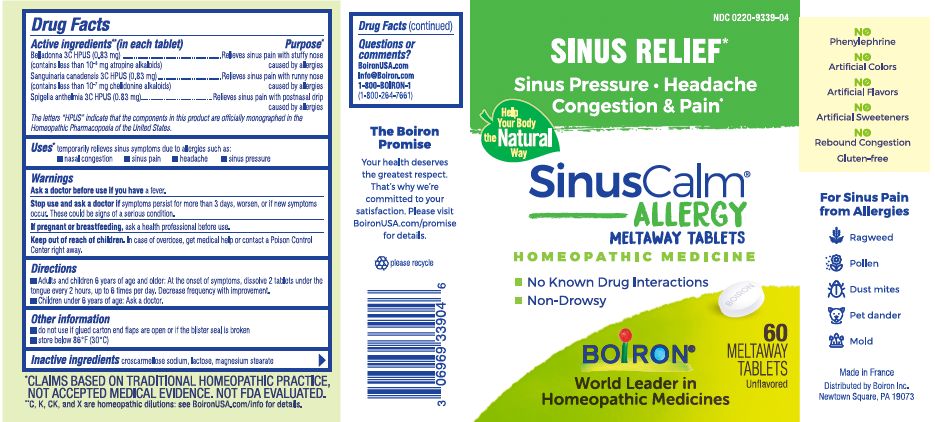 DRUG LABEL: SINUSCALM ALLERGY
NDC: 0220-9339 | Form: TABLET
Manufacturer: Boiron
Category: homeopathic | Type: HUMAN OTC DRUG LABEL
Date: 20230118

ACTIVE INGREDIENTS: ATROPA BELLADONNA 3 [hp_C]/1 1; SPIGELIA ANTHELMIA 3 [hp_C]/1 1; SANGUINARIA CANADENSIS ROOT 3 [hp_C]/1 1
INACTIVE INGREDIENTS: CROSCARMELLOSE SODIUM; MAGNESIUM STEARATE; LACTOSE, UNSPECIFIED FORM

SinusCalm Allergy

Active ingredients** (in each tablet)

Belladonna 3C HPUS (0.83 mg) (contains less than 10^-8 mg atropine alkaloids)

Sanguinaria canadensis 3C HPUS (0.83 mg) (contains less than 10^-7 mg chelidonine alkaloids)

Spigelia anthelmia 3C HPUS (0.83mg)

The letters "HPUS" indicate that the components in this product are officially monographed in the Homeopathic Pharmacopoeia of the United States.

Purpose*

Belladonna 3C HPUS (0.83 mg) ... Relieves sinus pain with stuffy nose caused by allergies

Sanguinaria canadensis 3C HPUS (0.83 mg) ... Relieves sinus pain with runny nose caused by allergies

Spigelia anthelmia 3C HPUS (0.83mg) ... Relieves sinus pain with postnasal drip caused by allergies

Uses*

temporarily relieves sinus symptoms due to allergies such as:

- nasal congestion
- sinus pain
- headache
- sinus pressure

Ask a doctor before use if you have a fever.

Stop use and ask a doctor if symptoms persist for more than 3 days, worsen, or if new symptoms occur. These could be signs of a serious condition.

PREGNANCY OR BREAST FEEDING

If pregnant or breastfeeding, ask a health professional before use.

Keep out of reach of children. In case of overdose, get medical help or contact a Poison Control Center right away.

DOSAGE AND ADMINISTRATION

Adults and children 6 years of age and older: At the onset of symptoms, dissolve 2 tablets under the tongue every 2 hours, up to 6 times per day. Decrease frequency with improvement.

Children under 6 years of age: Ask a doctor.

INACTIVE INGREDIENT

croscarmellose sodium, lactose, magnesium stearate

Sinus Relief*

Sinus Pressure Headache Congestion & Pain*

do not use if glued carton flaps are open or if the blister seal is broken

store below 86° F (30° C)

No Known Drug Interactions

Non-Drowsy

60 MELTAWAY TABLETS

Unflavored

No Phenylephrine

No Artificial Colors

No Artificial Flavors

No Artificial Sweeteners

No Rebound Congestion

Gluten-free

*CLAIMS BASED ON TRADITIONAL HOMEOPATHIC PRACTICE, NOT ACCEPTED MEDICAL EVIDENCE. NOT FDA EVALUATED.
*C,K,CK, and X are homeopathic dilutions: see BoironUSA.com/info for details.

QUESTIONS

BoironUSA.com

Info@Boiron.com

1-800-BOIRON-1

(1-800-264-7661)